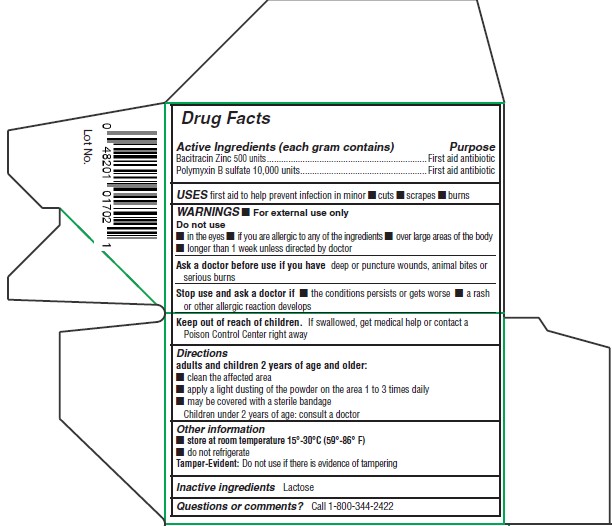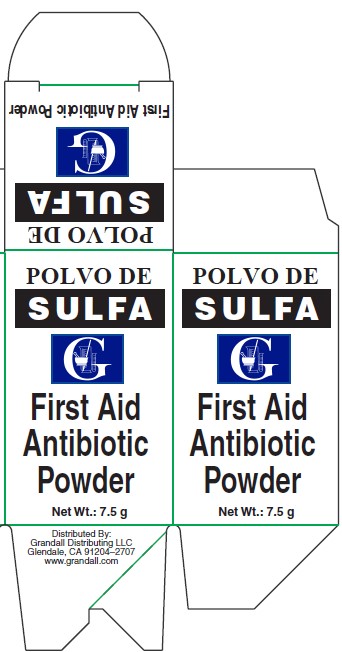 DRUG LABEL: POLVO DE SULFA FIRST AID ANTIBIOTIC
NDC: 48201-105 | Form: POWDER
Manufacturer: GRANDALL DISTRIBUTING, LLC
Category: otc | Type: HUMAN OTC DRUG LABEL
Date: 20251028

ACTIVE INGREDIENTS: BACITRACIN ZINC 500 [USP'U]/1 g; POLYMYXIN B SULFATE 10000 [USP'U]/1 g
INACTIVE INGREDIENTS: LACTOSE, UNSPECIFIED FORM

Grandall (as PLD) - POLVO DE SULFA POWDER (48201-105)

Active Ingredients:

BACITRACIN ZINC 500 UNITS

POLYMYXIN B SULFATE 10,000 UNITS

Purpose:

First aid antibiotic

Uses

First aid to help prevent infection in minor

- cuts
- scrapes
- burns

Warnings

- For external use only

Do not use

- in the eyes
- if you are allergic to any of the ingredients
- over large areas of the body
- longer than 1 week unless directed by doctor

Ask a doctor before use if you have deep or puncture wounds, animal bites or serious burns

Stop use and ask a doctor if

- the conditions persists or gets worse
- a rash or other allergic reaction develops

KEEP OUT OF REACH OF CHILDREN

Keep out of reach of childern.If swallowed, get medical help or contact a Poison Control Center immediately.

Directions

Adults and children 2 years of age and older:

- clean the affected area
- apply a light dusting of the powder on the area 1 to 3 times daily
- may be covered with a sterile bandage

Children under 2 years of age: consult a doctor

Inactive Ingredient

Lactose